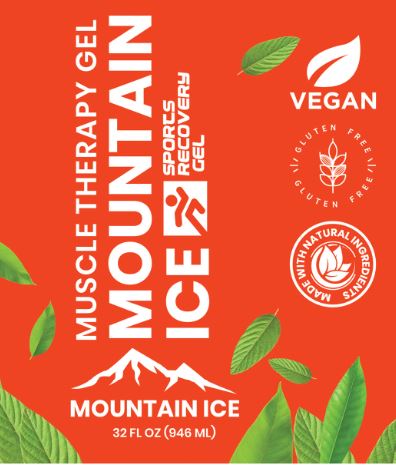 DRUG LABEL: Mountain Ice Sports

NDC: 72793-200 | Form: GEL
Manufacturer: Mountainside Medical Equipment, Inc.
Category: otc | Type: HUMAN OTC DRUG LABEL
Date: 20250721

ACTIVE INGREDIENTS: MENTHOL, UNSPECIFIED FORM 6 g/100 mL; CAMPHOR OIL 4 g/100 mL
INACTIVE INGREDIENTS: ALOE VERA LEAF; ARNICA MONTANA FLOWER; INDIAN FRANKINCENSE OIL; GREEN TEA LEAF; CARBOMER HOMOPOLYMER, UNSPECIFIED TYPE; TURMERIC OIL; DIMETHYL SULFONE; GLYCYRRHIZINATE DIPOTASSIUM; ETHYLHEXYLGLYCERIN; EUCALYPTUS OIL; GLYCERIN; ISOPROPYL ALCOHOL; ARGININE; LIMONENE, (+)-; MAGNESIUM SULFATE, UNSPECIFIED FORM; TEA TREE OIL; SPEARMINT OIL; NIACINAMIDE; ASIAN GINSENG; PHENOXYETHANOL; POLYSORBATE 20; .ALPHA.-TOCOPHEROL ACETATE; TROLAMINE; WATER; FD&C BLUE NO. 1

Mountain Ice Sports Recovery Gel

Active ingredients

Menthol 6%
Camphor 4%

Purpose

External Analgesic

Use:

Temporary relief of minor aches and pains of muscles and joints associated with osteoarthritis, rheumatoid arthritis, muscle strains, and sprains.

Warnings:

For external use only.

Flammable: keep away from excessive heat or open flame. Avoid contact with eyes or mucous membranes.

When using this product:

- Do not apply to wounds, damaged skin, or irritated skin.
- Do not apply with other creams, ointments, sprays or liniments.
- Stop use and ask a doctor if:Conditions worsen, skin irritation develops, or condition does not improve after 7 days, or clear up and recur.

Keep out the reach of children:

If accidentally swallowed get medical help or contact a Poison Control Center right away.

Directions:

Adults and children 2 years and older. Rub on the affected area evenly no more than 4 times per day. Children under 2 years: Consult with your doctor.

Inactive Ingredients:

Aloe Barbadensis Leaf Juice, Arnica Montana Flower Extract, Boswellia Serrata (Frankincense) Oil, Camellia Sinensis (Green Tea) Leaf Extract, Carbomer, Curcuma Longa (Turmeric) Root Oil, Dimethyl Sulfone, Dipotassium Glycyrrhizate, Ethylhexylglycerin, Eucalyptus Globulus (Eucalyptus) Leaf Oil, Glycerin, Isopropyl Alcohol, L-Arginine, Limonene, Magnesium Sulfate, Melaleuca Alternifolia (Tea Tree) Leaf Oil, Mentha Spicata (Spearmint) Oil, Niacinamide, Panax Ginseng Root Extract, Phenoxyethanol, Polysorbate 20, Tocopheryl Acetate, Triethanolamine, Water (Aqua), Blue 1 (CI 42090)

Package/Label Principal Display Panel

MUSCEL THERAPY GEL

MOUNTAIN ICE

SPORTS RECOVERYGEL

VEGAN
GLUTEN FREE \ ǀ / GLUTEN FREE \ ǀ /
MADE WITH NATURAL INGREDIENTS

MOUNTAIN ICE
32 FL OZ (946 ML)

Label